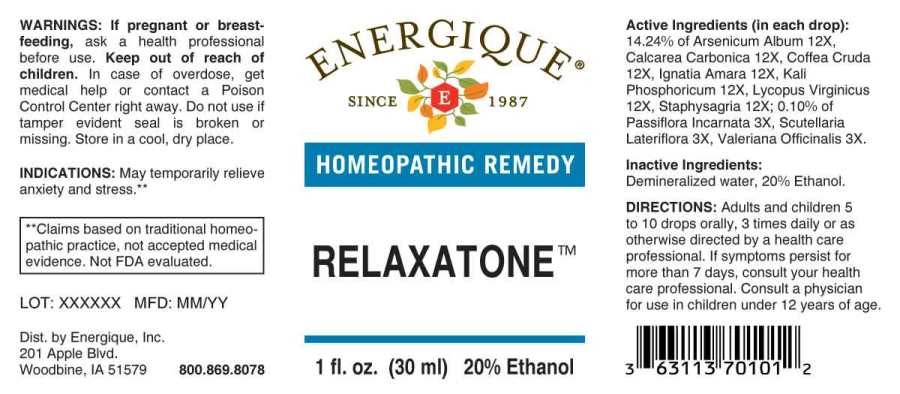 DRUG LABEL: Relaxatone
NDC: 44911-0077 | Form: LIQUID
Manufacturer: Energique, Inc.
Category: homeopathic | Type: HUMAN OTC DRUG LABEL
Date: 20241030

ACTIVE INGREDIENTS: PASSIFLORA INCARNATA FLOWERING TOP 3 [hp_X]/1 mL; SCUTELLARIA LATERIFLORA WHOLE 3 [hp_X]/1 mL; VALERIAN 3 [hp_X]/1 mL; ARSENIC TRIOXIDE 12 [hp_X]/1 mL; OYSTER SHELL CALCIUM CARBONATE, CRUDE 12 [hp_X]/1 mL; ARABICA COFFEE BEAN 12 [hp_X]/1 mL; STRYCHNOS IGNATII SEED 12 [hp_X]/1 mL; POTASSIUM PHOSPHATE, DIBASIC 12 [hp_X]/1 mL; LYCOPUS VIRGINICUS WHOLE 12 [hp_X]/1 mL; DELPHINIUM STAPHISAGRIA SEED 12 [hp_X]/1 mL
INACTIVE INGREDIENTS: WATER; ALCOHOL

DRUG FACTS:

ACTIVE INGREDIENTS:

(in each drop): 14.24% of Arsenicum Album 12X, Calcarea Carbonica 12X, Coffea Cruda 12X, Ignatia Amara 12X, Kali Phosphoricum 12X, Lycopus Virginicus 12X, Staphysagria 12X; 0.10% of Passiflora Incarnata 3X, Scutellaria Lateriflora 3X, Valeriana Officinalis 3X.

INDICATIONS:

May temporarily relieve anxiety and stress.

**Claims based on traditional homeopathic practice, not accepted medical evidence. Not FDA evaluated.

WARNINGS:

If pregnant or breast-feeding, ask a health professional before use.

Keep out of reach of children. In case of overdose, get medical help or contact a Poison Control Center right away.

Do not use if tamper evident seal is broken or missing. Store in a cool, dry place.

Keep out of reach of children. In case of overdose, get medical help or contact a Poison Control Center right away.

DIRECTIONS:

Adults and children 5 to 10 drops orally, 3 times daily or as otherwise directed by a health care professional. If symptoms persist for more than 7 days, consult your health care professional. Consult a physician for use in children under 12 years of age.

INDICATIONS:

May temporarily relieve anxiety and stress.

**Claims based on traditional homeopathic practice, not accepted medical evidence. Not FDA evaluated.

INACTIVE INGREDIENTS:

Demineralized water, 20% Ethanol.

QUESTIONS:

Dist. by Energique, Inc.

201 Apple Blvd

Woodbine, IA 51579

800-869-8078

PACKAGE LABEL DISPLAY:

ENERGIQUE

SINCE 1987

HOMEOPATHIC REMEDY

RELAXATONE

1 fl. oz. (30 ml)